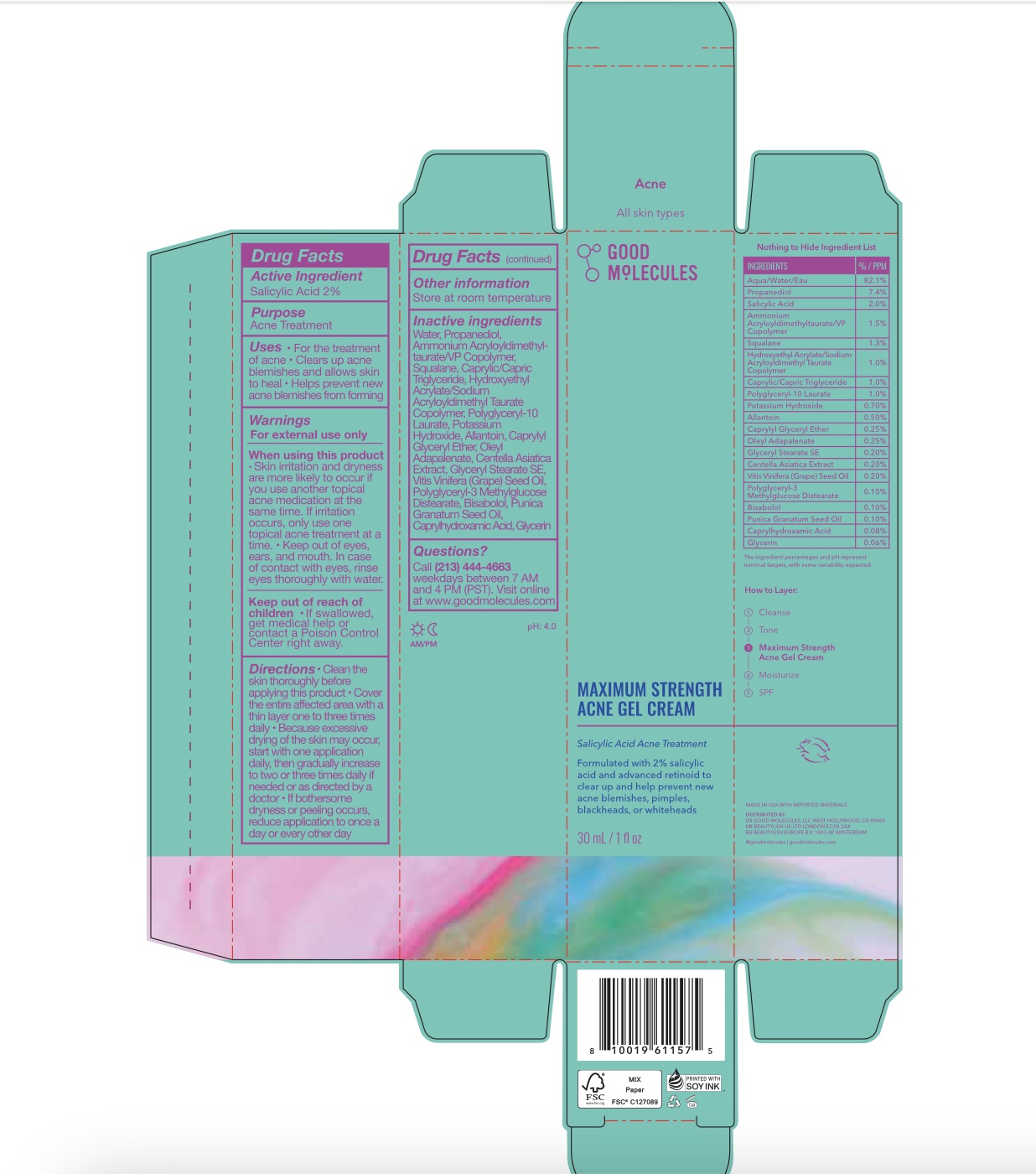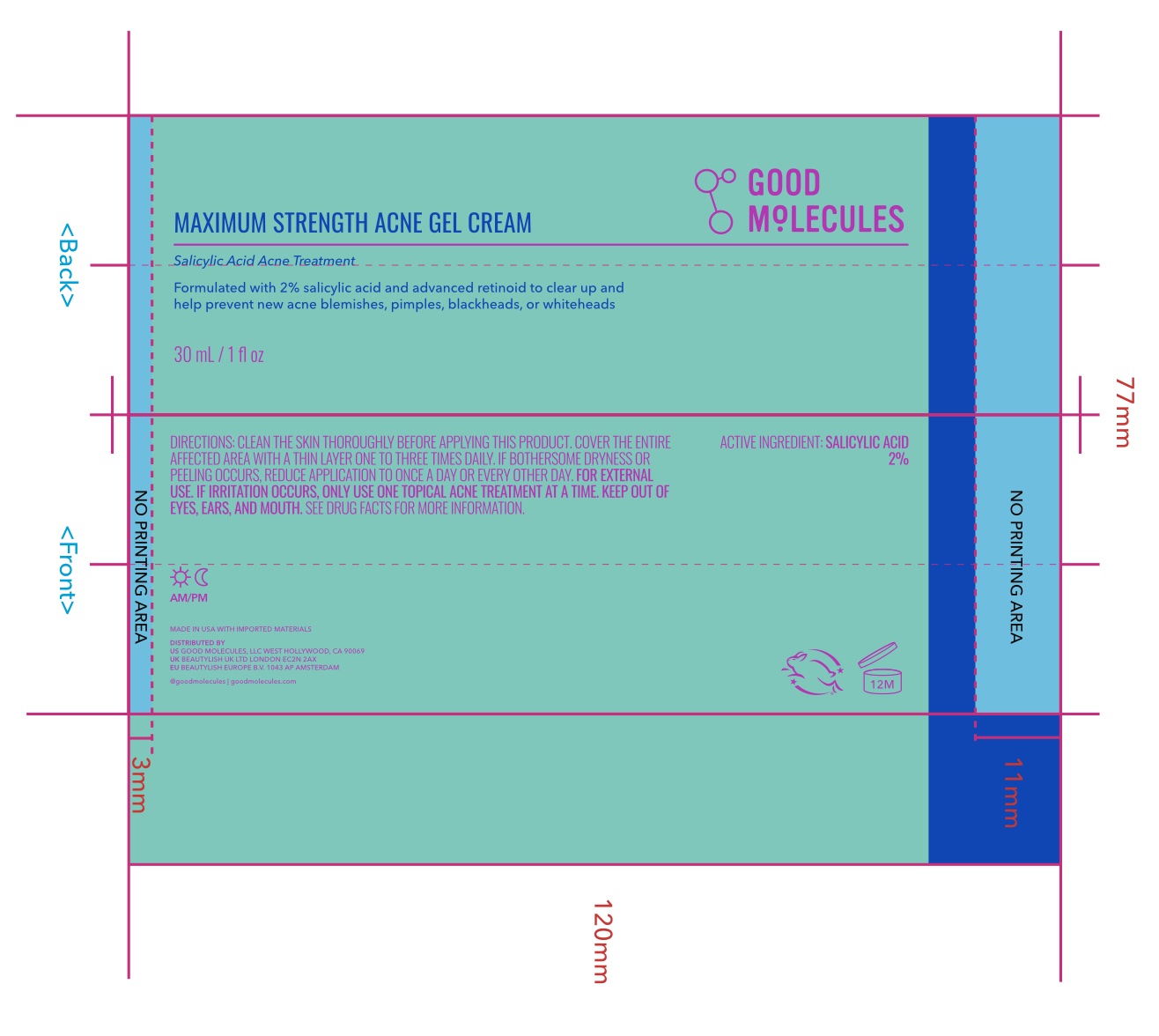 DRUG LABEL: Good Molecules Maximum Strength Acne Gel Cream
NDC: 82730-102 | Form: GEL
Manufacturer: Good Molecules, LLC
Category: otc | Type: HUMAN OTC DRUG LABEL
Date: 20251201

ACTIVE INGREDIENTS: SALICYLIC ACID 2 g/100 mL
INACTIVE INGREDIENTS: BISABOLOL; PROPANEDIOL; SQUALANE; GLYCERYL STEARATE SE; CAPRYLIC/CAPRIC TRIGLYCERIDE; CAPRYLYL GLYCERYL ETHER; ALLANTOIN; WATER; CENTELLA ASIATICA; VITIS VINIFERA SEED; OLEYL ADAPALENATE; POLYGLYCERYL-3 METHYLGLUCOSE DISTEARATE; POTASSIUM HYDROXIDE; PUNICA GRANATUM SEED OIL; CAPRYLHYDROXAMIC ACID; GLYCERIN; POLYGLYCERYL-10 LAURATE; AMMONIUM ACRYLOYLDIMETHYLTAURATE/VP COPOLYMER; HYDROXYETHYL ACRYLATE/SODIUM ACRYLOYLDIMETHYL TAURATE COPOLYMER (45000 MPA.S AT 1%)

Good Molecules Maximum Strength Acne Gel Cream

Purpose

Acne treatment

Use

For the treatment of acne. Clears up acne blemishes and allows skin to heal. Helps preveent new acne blemishes from forming

Active Ingredient

Salicylic Acid 2%

Directions

- Clean the skin thoroughly before applying this product
- Cover the entire affected area with a thin layer one to three times daily
- Because excessive drying of the skin may occur, start with one application daily, then gradually increase to two or three times daily if needed or as directed by a doctor
- If bothersome dryness or peeling occurs, reduce application to once a day or every other day

Warnings

For external use only

When using this product

- Skin irritation and dryness are more likely to occur if you use another topical acne medication at the same time. If irritation occurs, only use one topical acne treatment at a time.
- Keep out of eyes, ears, and mouth. In case of contact with eyes, rinse eyes thoroughly with water.

Keep out of reach of children section

- If swallowed, get medical help or contact a Poison Control Center right away.

When using this product

- Skin irritation and dryness are more likely to occur if you use another topical acne medication at the same time. If irritation occurs, only use one topical acne treatment at a time.
- Keep out of eyes, ears, and mouth. In case of contact with eyes, rinse eyes thoroughly with water.

INACTIVE INGREDIENT

Water, Propanediol, Ammonium Acryloyldimethyltaurate/VP Copolymer, Squalane, Caprylic/Capric Triglyceride, Hydroxyethyl Acrylate/Sodium Acryloyldimethyl Taurate Copolymer, Polyglyceryl-10 Laurate, Potassium Hydroxide, Allantoin, Caprylyl Glyceryl Ether, Oleyl Adapalenate, Centella Asiatica Extract, Glyceryl Stearate SE, Vitis Vinifera (Grape) Seed Oil, Polyglyceryl-3 Methylglucose Distearate, Bisabolol, Punica Granatum Seed Oil, Caprylhydroxamic Acid, Glycerin

Other Information

Store at room temperature

QUESTIONS

Call (213) 444-4663 weekdays between 7 AM and 4 PM (PST). Visit online at www.goodmolecules.com